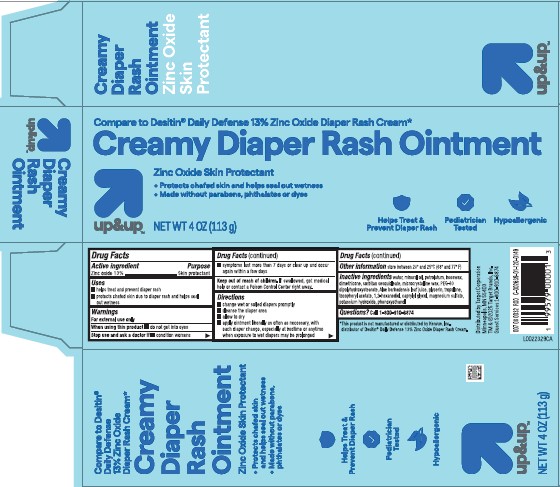 DRUG LABEL: Diaper Rash
NDC: 11673-226 | Form: CREAM
Manufacturer: Target Corporation
Category: otc | Type: HUMAN OTC DRUG LABEL
Date: 20260218

ACTIVE INGREDIENTS: ZINC OXIDE 130 mg/1 g
INACTIVE INGREDIENTS: WATER; MINERAL OIL; PETROLATUM; YELLOW WAX; DIMETHICONE; SORBITAN SESQUIOLEATE; MICROCRYSTALLINE WAX; PEG-30 DIPOLYHYDROXYSTEARATE; ALOE VERA LEAF; GLYCERIN; TROPOLONE; .ALPHA.-TOCOPHEROL ACETATE; 1,2-HEXANEDIOL; CAPRYLYL GLYCOL; MAGNESIUM SULFATE MONOHYDRATE; POTASSIUM HYDROXIDE; PHENOXYETHANOL

Up & Up 226.002/226AD
Creamy Diaper Rash Ointment

Active ingredient

Zinc oxide 13%

Purpose

Skin protectant

Uses

- helps treat and prevent diaper rash
- protects chafed skin due to diaper rash and helps seal out wetness

Warnings

For external use only

When using this product

- do not get into eyes

Stop use and ask a doctor if

- condition worsens
- symptoms last more than 7 days or clear up and occur again within a few days

Keep out of reach of children

If swallowed, get medical help or contact a Poison Control Center right away.

Directions

- change wet and soiled diaper promplty
- cleanse the diaper area
- allow to dry
- apply ointment liberally as often as necessary, with each diaper change, especially at bedtime or anytime when exposure to wet diapers may be prolonged

Other information

- store between 20º and 25ºC (68º and 77º F)

Inactive ingredients

water, mineral oil, petrolatum, beeswax, dimethicone, sorbitan sesquioleate, microcrystalline wax, PEG-30 dipolyhydroxystearate, Aloe barbadensis leaf juice, glycerin, tropolone, tocopheryl acetate, 1,2-hexanediol, caprylyl glycol, magnesium sulfate, potassium hydroxide, phenoxyethanol

Questions?

Call 1-800-910-6874

Disclaimer

*This product is not manufactured or distributed by Kenvue, Inc., distributor of Destin® Daily Defense 13% Zinc Oxide Diaper Rash Cream.

Adverse Reactions

Distributed by Target Corporation

Minneapolis, MN 55403

TM & ©2025 Target Brands, Inc.

Guest Services 1-800-910-6874

principal display panel

Compare to Destin® Daily Defense 13% Zinc Oxide Diaper Rash Cream*

Creamy Diaper Rash Ointment

Zinc Oxide Skin Protectant

- Protects chafed skin and helps seal out wetness
- Made without parabens, phthalates or dyes

Helps Treat & Prevent Diaper Rash

Pediatrician Tested

Hypoallengenic

up & up™

NET WT 4 OZ (113 g)